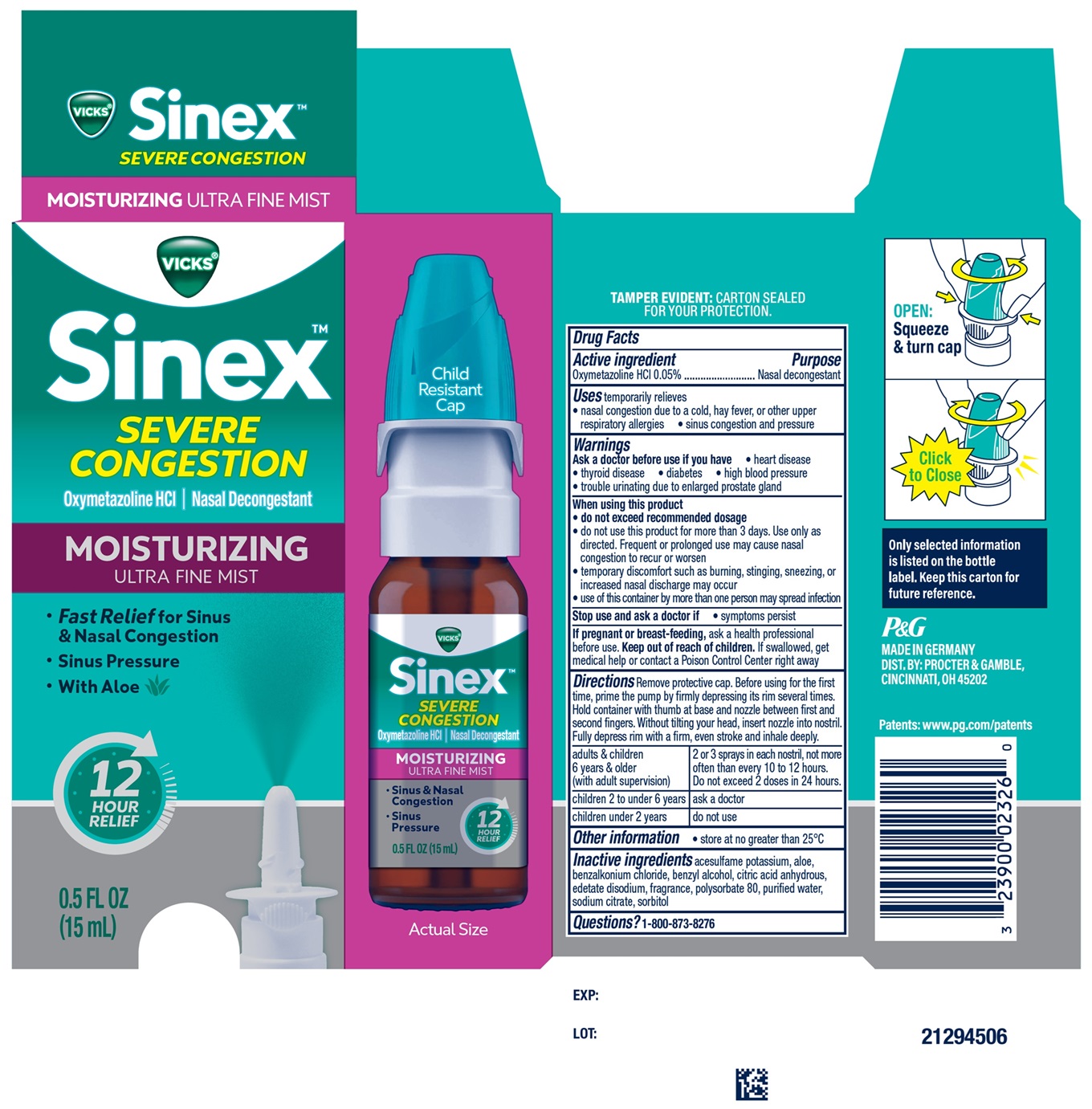 DRUG LABEL: Vicks Sinex SEVERECONGESTION
NDC: 64336-004 | Form: SPRAY
Manufacturer: Procter & Gamble Manufacturing GmbH
Category: otc | Type: HUMAN OTC DRUG LABEL
Date: 20251218

ACTIVE INGREDIENTS: OXYMETAZOLINE HYDROCHLORIDE 0.0005 g/1 mL
INACTIVE INGREDIENTS: ACESULFAME POTASSIUM; ALOE; BENZALKONIUM CHLORIDE; BENZYL ALCOHOL; EDETATE DISODIUM; POLYSORBATE 80; WATER; SODIUM CITRATE; SORBITOL; ANHYDROUS CITRIC ACID

Vicks®Sinex™ SEVERE CONGESTION, MOISTURIZING Ultra Fine Mist

Drug Facts

Active ingredient

Oxymetazoline HCl 0.05%

Purpose

Nasal decongestant

Usestemporarily relieves

- nasal congestion due to a cold, hay fever, or other upper respiratory allergies
- sinus congestion and pressure

Warnings

Ask a doctor before use if you have

- heart disease
- thyroid disease
- diabetes
- high blood pressure
- trouble urinating due to enlarged prostate gland

When using this product

- do not exceed recommended dosage
- do not use this product for more than 3 days. Use only as directed. Frequent or prolonged use may cause nasal congestion to recur or worsen
- temporary discomfort such as burning, stinging, sneezing, or increased nasal discharge may occur
- use of this container by more than one person may spread infection

Stop use and ask a doctor if

- symptoms persist.

If pregnant or breast-feeding,

ask a health professional before use.

Keep out of reach of children.

OVERDOSAGE

If swallowed, get medical help or contact a Poison Control Center right away

Directions

Remove protective cap. Before using for the first time, prime the pump by firmly depressing its rim several times. Hold container with thumb at base and nozzle between first and second fingers. Without tilting your head, insert nozzle into nostril. Fully depress rim with a firm, even stroke and inhale deeply.

adults & children 6 yrs. & older (with adult supervision) | 2 or 3 sprays in each nostril, not more often than every 10 to 12 hours. Do not exceed 2 doses in 24 hours.
children 2 to under 6 yrs. | ask a doctor
children under 2 yrs. | do not use

Other information

- store at no greater than 25°C

Inactive ingredients

acesulfame potassium, aloe, benzalkonium chloride, benzyl alcohol, citric acid anhydrous, edetate disodium, fragrance, polysorbate 80, purified water, sodium citrate, sorbitol.

Questions?

1-800-873-8276

Only selected information is listed on the bottle label. Keep this carton for future reference.

TAMPER EVIDENT:CARTON SEALED FOR YOUR PROTECTION.

MADE IN GERMANY

DIST. BY PROCTER & GAMBLE,

CINCINNATI OH 45202

PRINCIPAL DISPLAY PANEL - 15 ml Bottle Carton

VICKS®

Sinex™ SEVERE CONGESTION

Oxymetazoline HCl Nasal Decongestant

MOISTURIZING ULTRA FINE MIST

- Fast Relief for Sinus & Nasal Congestion
- Sinus Pressure
- With Aloe

12 HOUR RELIEF

0.5 FL OZ (15 mL)